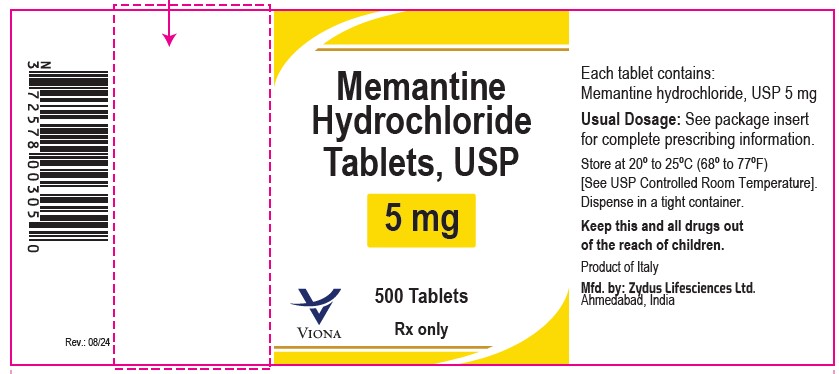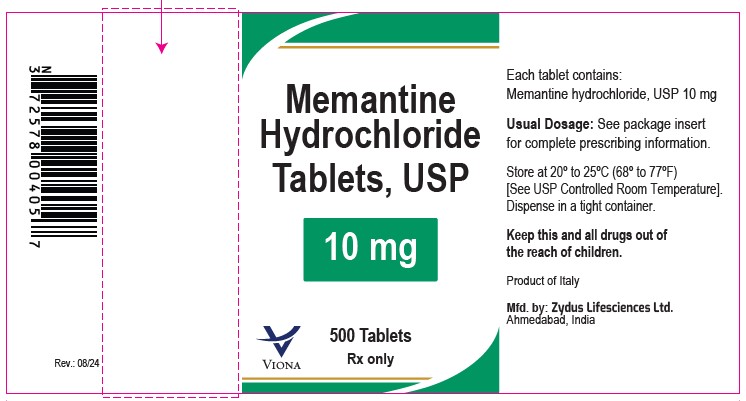 DRUG LABEL: Memantine Hydrochloride
NDC: 70771-1119 | Form: TABLET, FILM COATED
Manufacturer: Zydus Lifesciences Limited
Category: prescription | Type: HUMAN PRESCRIPTION DRUG LABEL
Date: 20240816

ACTIVE INGREDIENTS: MEMANTINE HYDROCHLORIDE 5 mg/1 1
INACTIVE INGREDIENTS: SILICON DIOXIDE; CROSCARMELLOSE SODIUM; DIBASIC CALCIUM PHOSPHATE DIHYDRATE; HYPROMELLOSES; CELLULOSE, MICROCRYSTALLINE; MAGNESIUM STEARATE; POVIDONE; TALC; TITANIUM DIOXIDE; POLYETHYLENE GLYCOL, UNSPECIFIED

MEMANTINE HYDROCHLORIDE TABLETS

PACKAGE LABEL.PRINCIPAL DISPLAY PANEL

NDC 70771-1119-5 in bottle of 500 tablets

Memantine Hydrochloride Tablets USP, 5 mg

Rx only

500 tablets

NDC 70771-1120-5 in bottle of 500 tablets

Memantine Hydrochloride Tablets USP, 10 mg

Rx only

500 tablets